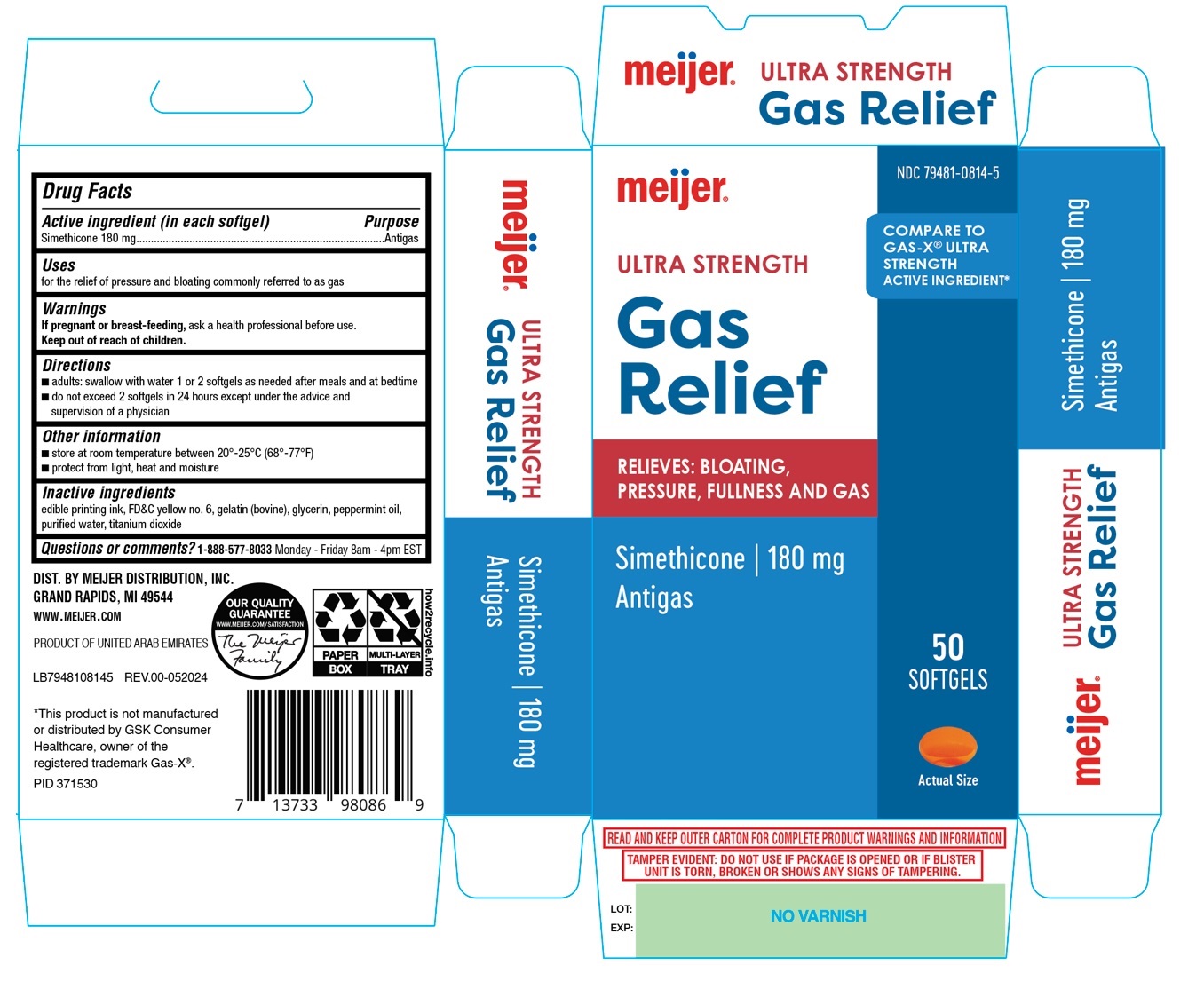 DRUG LABEL: meijer ULTRA STRENGTH Gas Relief SOFTGEL
NDC: 79481-0814 | Form: CAPSULE, LIQUID FILLED
Manufacturer: Meijer, Inc.
Category: otc | Type: HUMAN OTC DRUG LABEL
Date: 20240906

ACTIVE INGREDIENTS: DIMETHICONE, UNSPECIFIED 180 mg/1 1
INACTIVE INGREDIENTS: FD&C YELLOW NO. 6; GELATIN TYPE B BOVINE (230 BLOOM); GLYCERIN; PEPPERMINT OIL; WATER; TITANIUM DIOXIDE

meijer ULTRA STRENGTH Gas Relief SOFTGEL

Active ingredient (in each softgel)

Simethicone 180 mg

Purpose

Antigas

Uses

for the relief of pressure and bloating commonly referred to as gas

Warnings

If pregnant or breast-feeding, ask a health professional before use.

Keep out of reach of children.

Directions

• adults: swallow with water 1 or 2 softgels as needed after meals and at bedtime
• do not exceed 2 softgels in 24 hours except under the advice and supervision of a physician

Other information

• store at room temperature 20°-25°C (68°-77°F)
• protect from light, heat and moisture

Inactive ingredients

edible printing ink, FD&C yellow no. 6, gelatin (bovine), glycerin, peppermint oil, purified water, titanium dioxide

Questions or comments?

1-888-577-8033 Monday - Friday 8am - 4pm EST

COMPARE TO GAS-X® ULTRA STRENGHT ACTIVE INGREDIENT*

RELIEVES: BLOATING,

PRESSURE, FULLNESS AND GAS

DIST. BY MEIJER DISTRIBUTION, INC.
GRAND RAPIDS, MI 49544

WWW.MEIJER.COM

PRODUCT OF UNITED ARAB EMIRATES

*This product is not manufactured or distributed by GSK consumer Healthcare, owner of the registered trademark GAS-X®

READ AND KEEP OUTER CARTON FOR COMPLETE PRODUCT WARNINGS AND INFORMATION

TAMPER EVIDENT: DO NOT USE IF PACKAGE IS OPENED OR IF BLISTER UNIT IS TORN, BROKEN OR SHOWS ANY SIGNS OF TAMPERING.